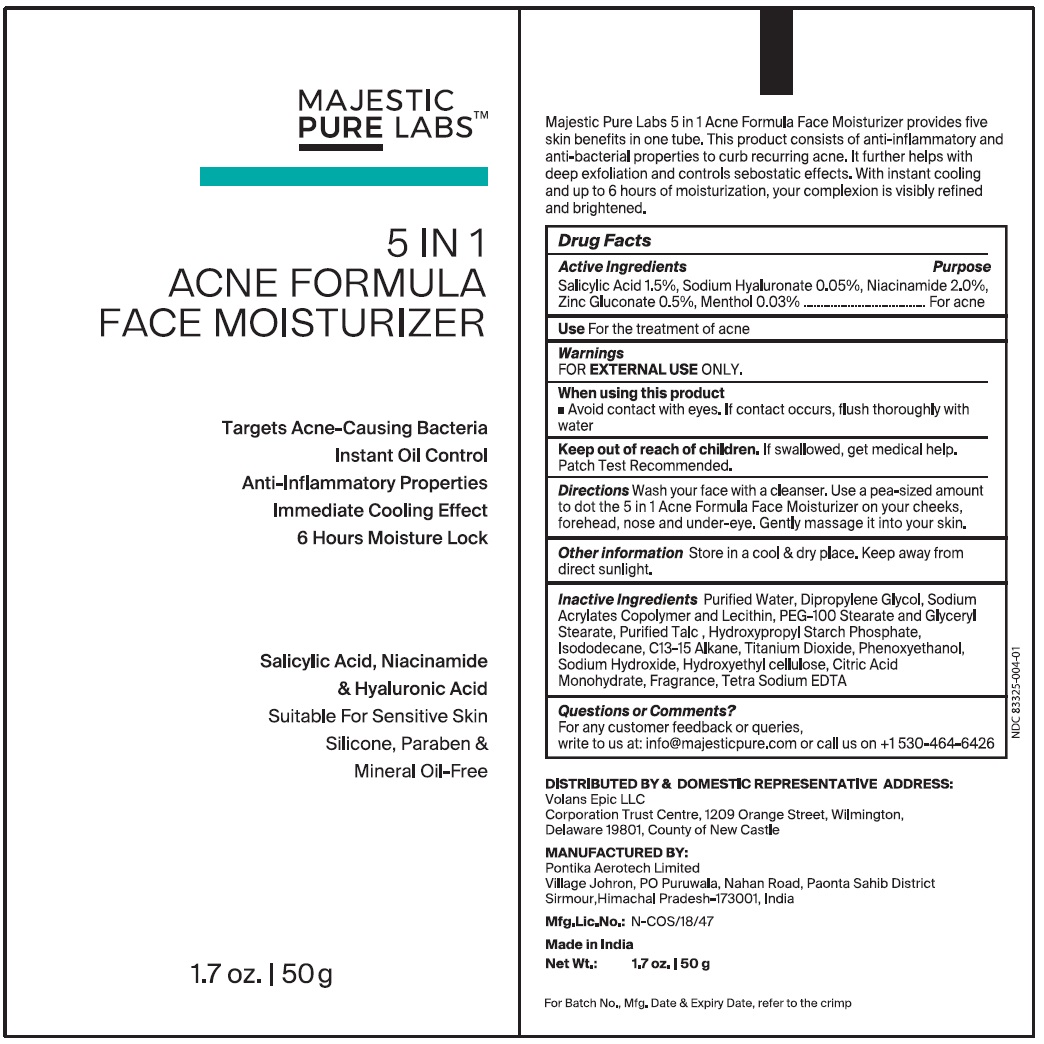 DRUG LABEL: ACNE FORMULA
NDC: 83325-004 | Form: CREAM
Manufacturer: Volans Epic LLC
Category: otc | Type: HUMAN OTC DRUG LABEL
Date: 20240207

ACTIVE INGREDIENTS: SALICYLIC ACID 1.5 g/50 g; HYALURONATE SODIUM 0.05 g/50 g; NIACINAMIDE 2 g/50 g; ZINC GLUCONATE 0.5 g/50 g; MENTHOL 0.03 g/50 g
INACTIVE INGREDIENTS: WATER; DIPROPYLENE GLYCOL; SODIUM ACRYLATE; GLYCERYL STEARATE/PEG-100 STEARATE; TALC; HYDROXYPROPYL CORN STARCH (5% SUBSTITUTION BY WEIGHT); ISODODECANE; C13-15 ALKANE; TITANIUM DIOXIDE; PHENOXYETHANOL; SODIUM HYDROXIDE; HYDROXYMETHYL CELLULOSE; CITRIC ACID MONOHYDRATE; FRAGRANCE 13576; EDETATE SODIUM

5 IN 1
ACNE FORMULA
FACE MOISTURIZER
Targets Acne-Causing Bacteria
Instant Oil Control
Anti-Inflammatory Properties
Immediate Cooling Effect
6 Hours Moisture Lock
Salicylic Acid, Niacinamide
& Hyaluronic Acid
Suitable For Sensitive Skin
Silicone, Paraben &
Mineral Oil-Free

Active Ingredients Purpose

Salicylic Acid 1.5%, Sodium Hyaluronate 0.05%, Niacinamide 2.0%, Zinc Gluconate 0.5%, Menthol 0.03% ---------------For acne

Use

For the treatment of acne

Warnings

FOR EXTERNAL USEONLY.

When using this product

■ Avoid contact with eyes. If contact occurs, flush thoroughly with water

Keep out of reach of children.If swallowed, get medical help.
Patch Test Recommended.

DIRECTIONS

Wash your face with a cleanser. Use a pea-sized amount to dot the 5 in 1 Acne Formula Face Moisturizer on your cheeks, forehead, nose and under-eye. Gently massage it into your skin.

Other lnformation

Store in a cool & dry place. Keep away from direct sunlight.

Inactive Ingredients

Purified Water, Dipropylene Glycol, Sodium Acrylates Copolymer and Lecithin, PEG-100 Stearate and Glyceryl Stearate, Purified Talc, Hydroxypropyl Starch Phosphate, Isododecane, C13-15 Alkane, Titanium Dioxide, Phenoxyethanol, Sodium Hydroxide, Hydroxyethyl cellulose, Citric Acid Monohydrate, Fragrance, Tetra Sodium EDTA

Questions or Comments?

For any customer feedback or queries,
write to us at: info@majesticpure.com or call us on +1 530-464-6426

DISTRIBUTED BY & DOMESTIC REPRESENTATIVE ADDRESS:
Volans Epic LLC
Corporation Trust Center, 1209 Orange Street, Wilmington,
Delaware 19801, Country of New Castle

MANUFACTURED BY:
Pontika Aerotech Limited
Village Johron, PO Puruwala, Nahan Road, Paonta Sahib District
Sirmour, Himachal Pradesh-173001, India

Mfg.Lic.No.:N-COS/18/47

Made in India